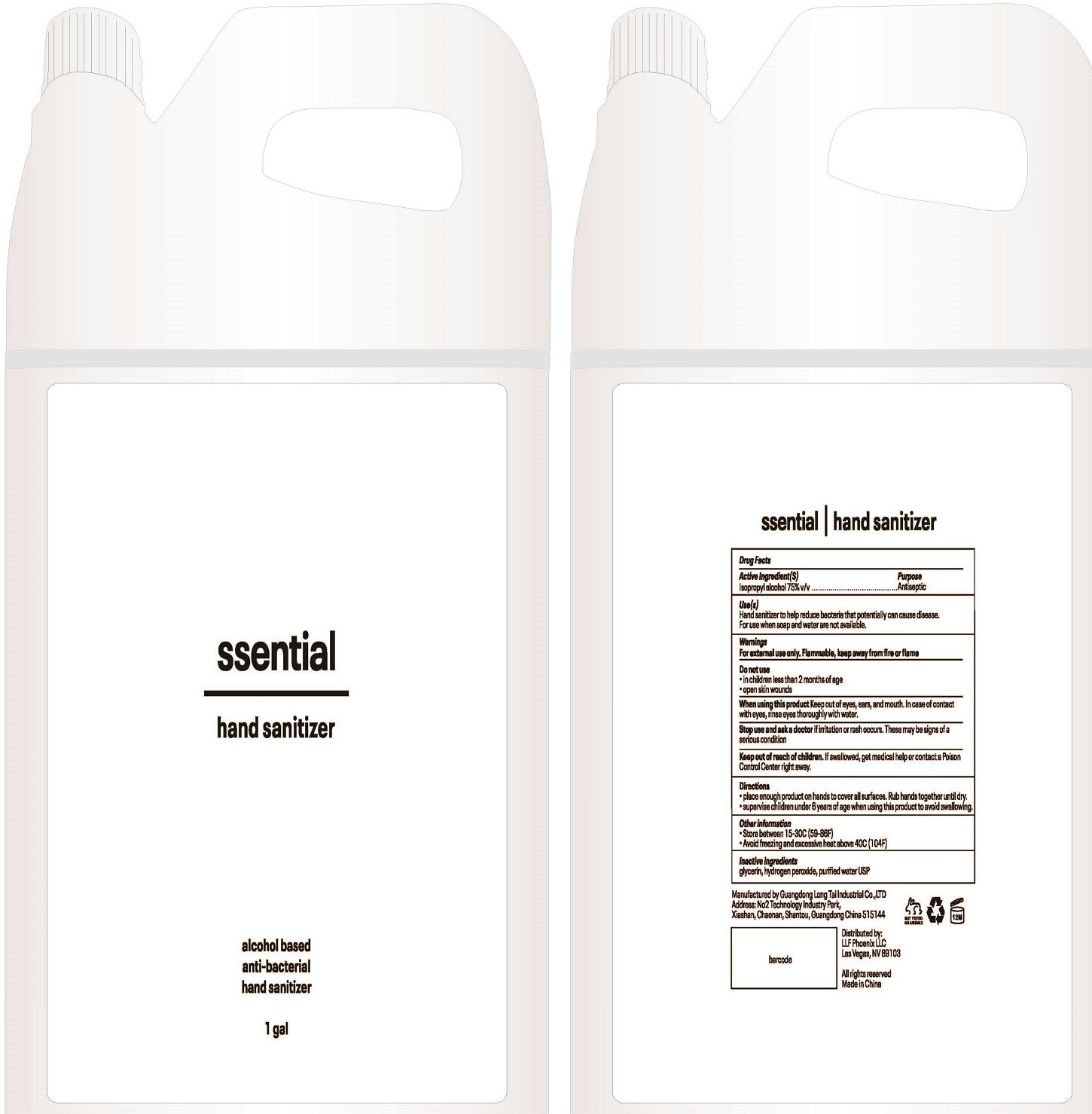 DRUG LABEL: ssential hand sanitizer
NDC: 52807-010 | Form: LIQUID
Manufacturer: Guangdong Longtai Industry Co.,Ltd.
Category: otc | Type: HUMAN OTC DRUG LABEL
Date: 20200518

ACTIVE INGREDIENTS: ISOPROPYL ALCOHOL 3750 mL/5000 mL
INACTIVE INGREDIENTS: HYDROGEN PEROXIDE; GLYCERIN; WATER

DOSAGE AND ADMINISTRATION

Store between 15-30°C(59-86°F).Avoid freezing and excessive heat above 40°C(104°F).

INACTIVE INGREDIENT

Glycerin, hydrogen peroxide， purified water UPS

INDICATIONS AND USAGE

1.Place enough product on hands to cover all surfaces. Rub hands together until dry.
2.Supervise children under 6 year of age when using this product to avoid swallowing.

ACTIVE INGREDIENT

Isopropyl alcohol

keep out of reach of children

PURPOSE

Disinfection
Sterilization
No Rinseing

WARNINGS

For extemal use only,Flammeble, keep away from fire or flame.